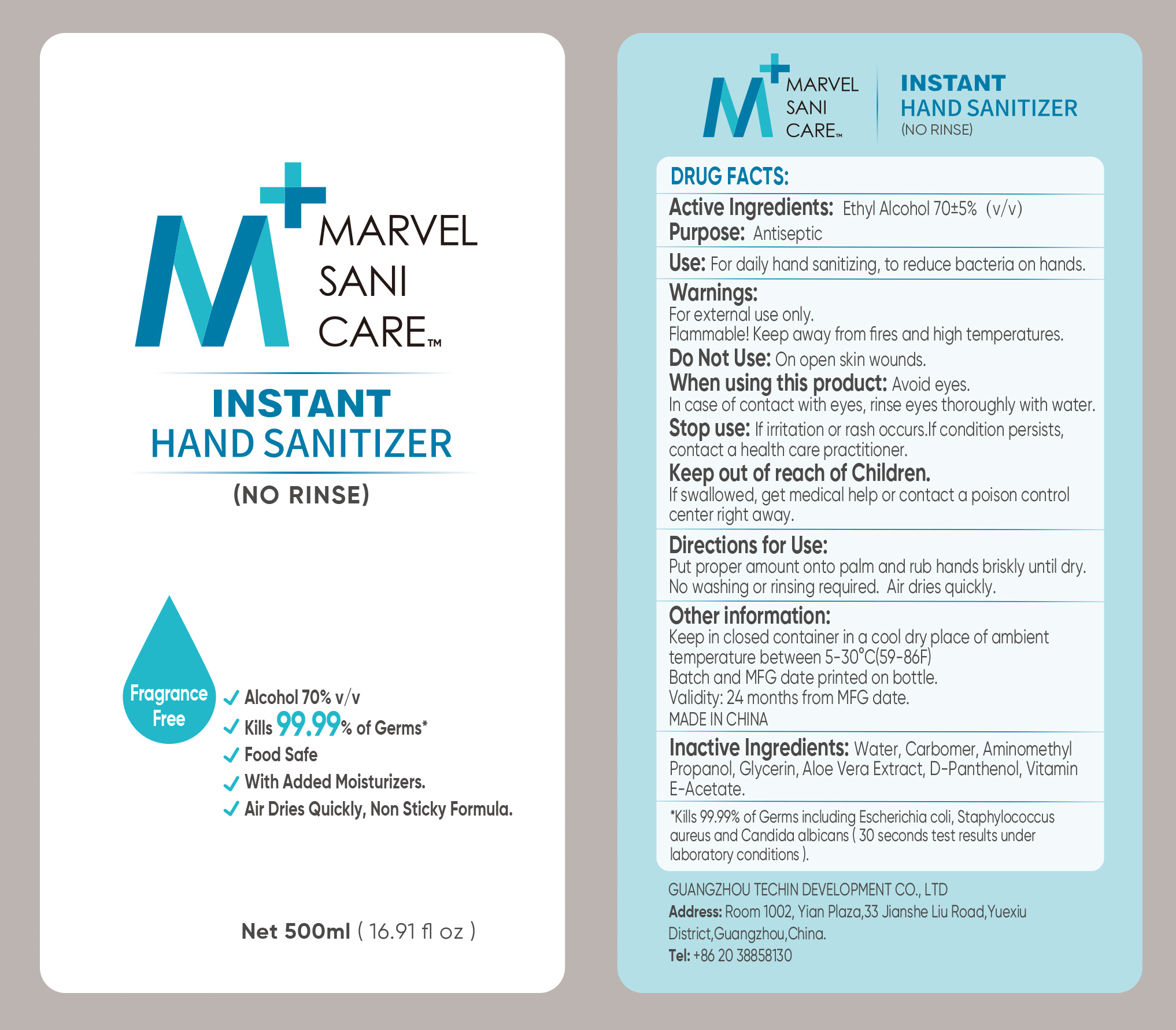 DRUG LABEL: M MARVEL SANI CARE Instant Hand Sanitizer
NDC: 80107-001 | Form: GEL
Manufacturer: GUANGZHOU TECHIN DEVELOPMENT CO., LTD
Category: otc | Type: HUMAN OTC DRUG LABEL
Date: 20220303

ACTIVE INGREDIENTS: ALCOHOL 70 mL/100 mL
INACTIVE INGREDIENTS: WATER; CARBOMER 940; GLYCERIN; ALOE VERA WHOLE; .ALPHA.-TOCOPHEROL ACETATE; AMINOMETHYLPROPANOL; PANTHENOL

Active Ingredient

Ethyl Alcohol 70% v/v

Purpose

Antiseptic

Use

For daily hand sanitizing, to reduce bateria on hands

Warnings

For external use only

Flammable. Keep away from fires and high temperature

Do not use on open skin wounds

Avoid eyes. In case of contact with eyes, rinse eyes thoroughly with water.

Stop use if irritation or rash occurs, if condition persists, contact a healthcare proactitioner

Keep out of reach of children. If swallowed, get medical help or contact a Poison Control Center right away.

Directions

- Put proper amount onto palms and rub hands briskly until dry.
- No washing or rinsing required. Air dries quickly

Other information

Keep in closed container in a cool dry place of ambient temperature between 5-30C (59-86F)

Batch and MFG date printed on bottle

Validity: 24 mounths from MFG date

Made in China

Inactive ingredients

Water, Aminomethyl propanol, aloe vera extract, glycerin, carbomer, D-Panthenol, vitamin E